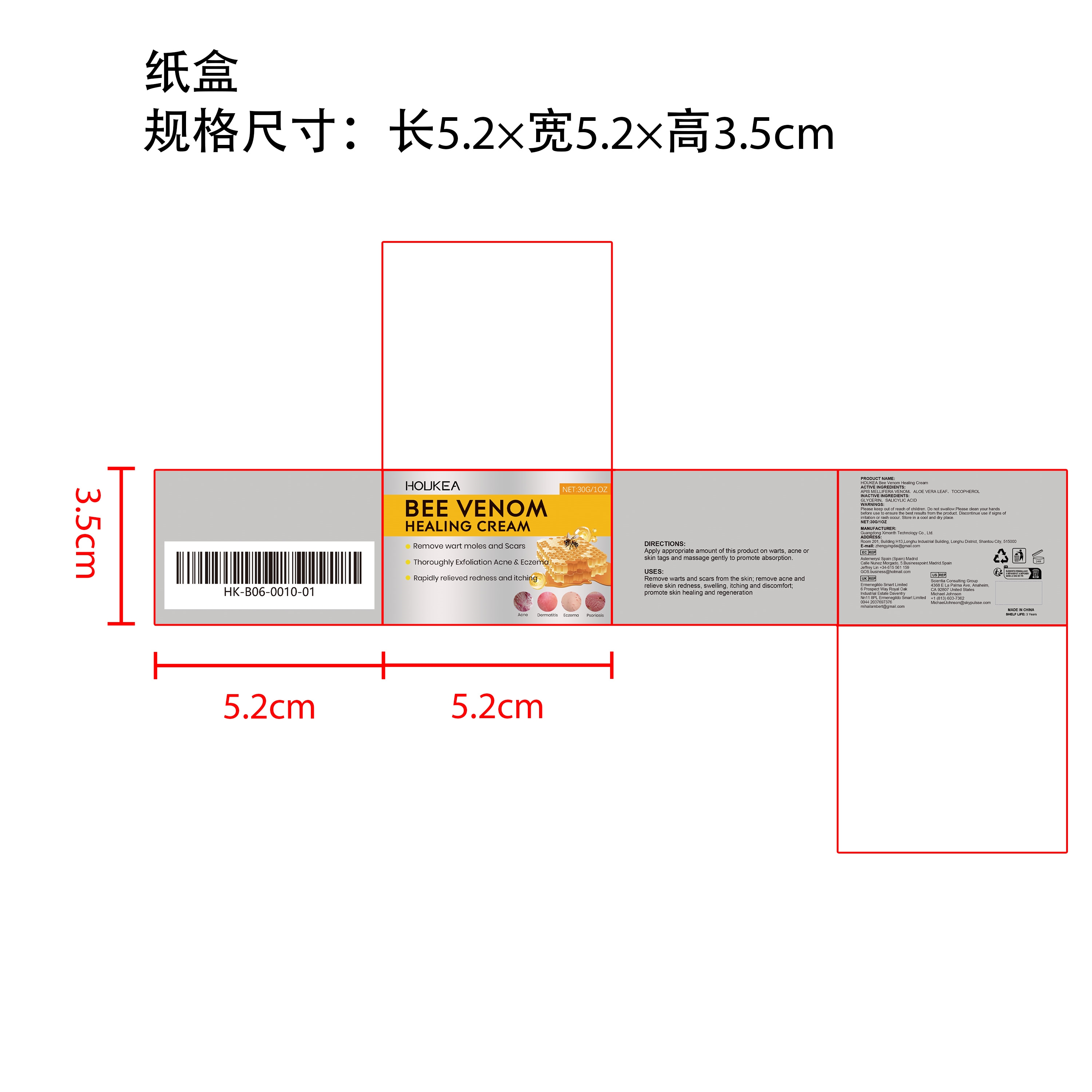 DRUG LABEL: HOUKEA Bee Venom Healing Cream
NDC: 84660-086 | Form: CREAM
Manufacturer: Guangdong Ximonth Technology Co., Ltd.
Category: otc | Type: HUMAN OTC DRUG LABEL
Date: 20241028

ACTIVE INGREDIENTS: ALOE VERA LEAF 3 g/30 g; APIS MELLIFERA VENOM 9 g/30 g; TOCOPHEROL 4.5 g/30 g
INACTIVE INGREDIENTS: GLYCERIN 4.5 g/30 g; SALICYLIC ACID 9 g/30 g

ACTIVE INGREDIENTS

APIS MELLIFERA VENOM, ALOE VERA LEAF,TOCOPHEROL

PURPOSE

Remove warts and scars from the skin; remove acne and relieve skin redness, swelling, itching and discomfort; promote skin healing and regeneration

USES

Apply appropriate amount of this product on warts, acne or skin tags and massage gently to promote absorption.

WARNINGS

Please keep out of reach of children. Do not swallow Please dean your hands before use to ensure the best results from the product. Discontinue use if signs of irritation or rash occur. Store in a cool and dry place.

STOP USE

Discontinue use if signs of irritation or rash occur.

DO NOT USE

Discontinue use if signs of irritation or rash occur.

KEEP OUT OF REACH OF CHILDREN

Please keep out of reach of children. Do not swallow

STORAGE AND HANDLING

Store in a cool and dry place.

INACTIVE INGREDIENT

GLYCERIN、SALICYLIC ACID